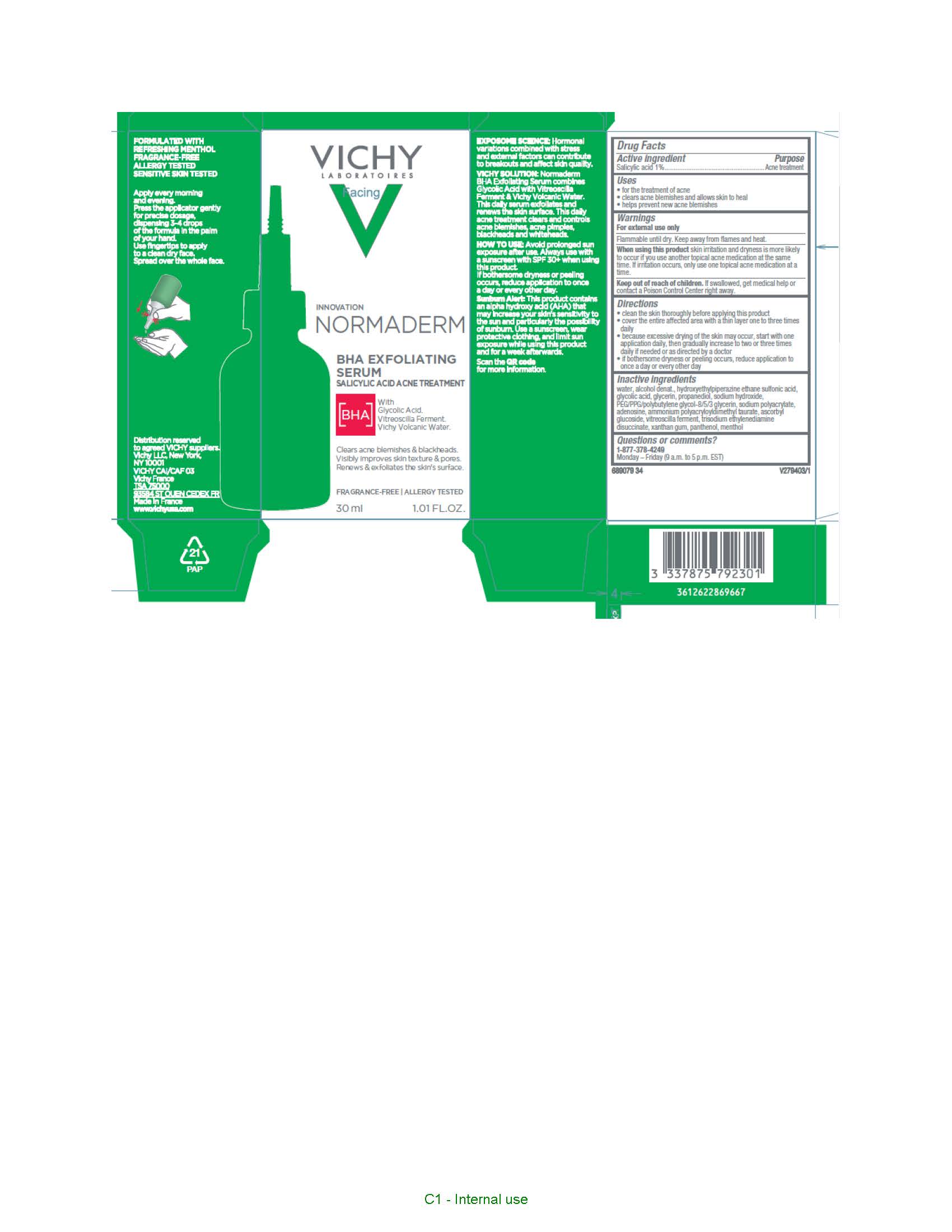 DRUG LABEL: Vichy Laboratoires Normaderm BHA Exfoliating Serum Acne Treatment
NDC: 49967-230 | Form: LOTION
Manufacturer: L'Oreal USA Products Inc
Category: otc | Type: HUMAN OTC DRUG LABEL
Date: 20231211

ACTIVE INGREDIENTS: SALICYLIC ACID 10 mg/1 mL
INACTIVE INGREDIENTS: WATER; ALCOHOL; HYDROXYETHYLPIPERAZINE ETHANE SULFONIC ACID; GLYCOLIC ACID; GLYCERIN; PROPANEDIOL; SODIUM HYDROXIDE; SODIUM POLYACRYLATE (2500000 MW); ADENOSINE; AMMONIUM POLYACRYLOYLDIMETHYL TAURATE (55000 MPA.S); ASCORBYL GLUCOSIDE; VITREOSCILLA LYSATE; TRISODIUM ETHYLENEDIAMINE DISUCCINATE; XANTHAN GUM; PANTHENOL; MENTHOL

Drug Facts

Active ingredient

Salicylic acid 1%

Purpose

Acne treatment

Uses

- for the treatment of acne
- clears acne blemishes and allows skin to heal
- helps prevent new acne blemishes

Warnings

For external use only

Flammable until dry.

Keep away from flames and heat.

When using this product

skin irritation and dryness is more likely to occur if you use another topical acne medication at the same time. If irritation occurs, only use one topical acne medication at a time.

Keep out of reach of children.

If swallowed, get medical help or contact a Poison Control Center right away.

Directions

- cleanse the skin thoroughly before applying this product
- cover the entire affected area with a thin layer one to three times daily
- because too much drying of the skin may occur, start with one application daily, then gradually increase to two or three times daily if needed or as directed by a doctor
- if bothersome dryness or peeling occurs, reduce application to once a day or every other day

Inactive ingredients

water, alcohol denat., hydroxyethylpiperazine ethane sulfonic acid, glycolic acid, glycerin, propanediol, sodium hydroxide, PEG/PPG/polybutylene glycol-8/5/3 glycerin, sodium polyacrylate, adenosine, ammonium polyacryloyldimethyl taurate, ascorbyl glucoside, vitreoscilla ferment, trisodium ethylenediamine disuccinate, xanthan gum, panthenol, menthol

Questions or comments?

Call toll free 1-877-37-VICHY (84249)

Monday – Friday (9 a.m. to 5 p.m. EST)